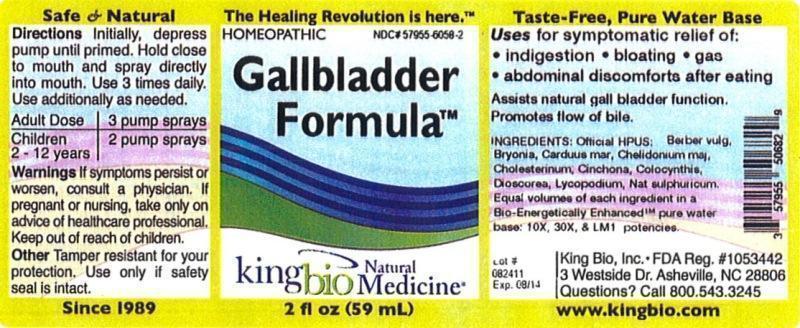 DRUG LABEL: Gallbladder Formula
                
                
                
NDC: 57955-6058 | Form: LIQUID
Manufacturer: King Bio Inc.
Category: homeopathic | Type: HUMAN OTC DRUG LABEL
Date: 20120905

ACTIVE INGREDIENTS: BERBERIS VULGARIS ROOT BARK 10 [hp_X]/59 mL; BRYONIA ALBA ROOT 10 [hp_X]/59 mL; SILYBUM MARIANUM SEED 10 [hp_X]/59 mL; CHELIDONIUM MAJUS 10 [hp_X]/59 mL; CHOLESTEROL 10 [hp_X]/59 mL; CINCHONA OFFICINALIS BARK 10 [hp_X]/59 mL; CITRULLUS COLOCYNTHIS FRUIT PULP 10 [hp_X]/59 mL; DIOSCOREA VILLOSA TUBER 10 [hp_X]/59 mL; LYCOPODIUM CLAVATUM SPORE 10 [hp_X]/59 mL; SODIUM SULFATE 10 [hp_X]/59 mL
INACTIVE INGREDIENTS: WATER

Gallbladder Formula

Active Ingredients

Official HPUS: Barberis vulgaris, Bryonia, Carduus marianus, Chelidonium majus, Cholesterinum, Cinchona officinalis, Colocynthis, Dioscorea villosa, Lycopodium clavatum, Natrum sulphuricum.

Inactive Ingredient

Equal volumes of each ingredient in a Bio-Energetically Enhanced pure water base: 10X, 30X, and LM1 potencies.

Purpose

Uses for symptomatic relief of:

- Indigestion
- bloating
- gas
- abdominal discomforts after eating

Assists natural gall bladder function.
Promotes flow of bile.

Warnings

If symptoms persist or worsen, consult a physician. If pregnant or nursing, take only on advice of healthcare professional. Keep out of reach of children.

Other: Tamper resistant for your protection. Use only if safety seal is intact.

Keep out of reach of children.

Dosage and Administration

Initially, depress pump until primed. Hold close to mouth and spray directly into mouth. Use 3 times daily. Use additionally as needed.

Adult Dose 3 pump sprays

Children 2 - 12 years 2 pump sprays

Indications and Usage

Uses for symptomatic relief of: indigestion, bloating, gas, abdominal discomforts after eating.

Assists natural gall bladder function.

Promotes flow of bile.

PACKAGE LABEL

King Bio Inc.

3 Westside Drive

Asheville, NC 28806

Questions? Call 800.543.3245

www.kingbio.com